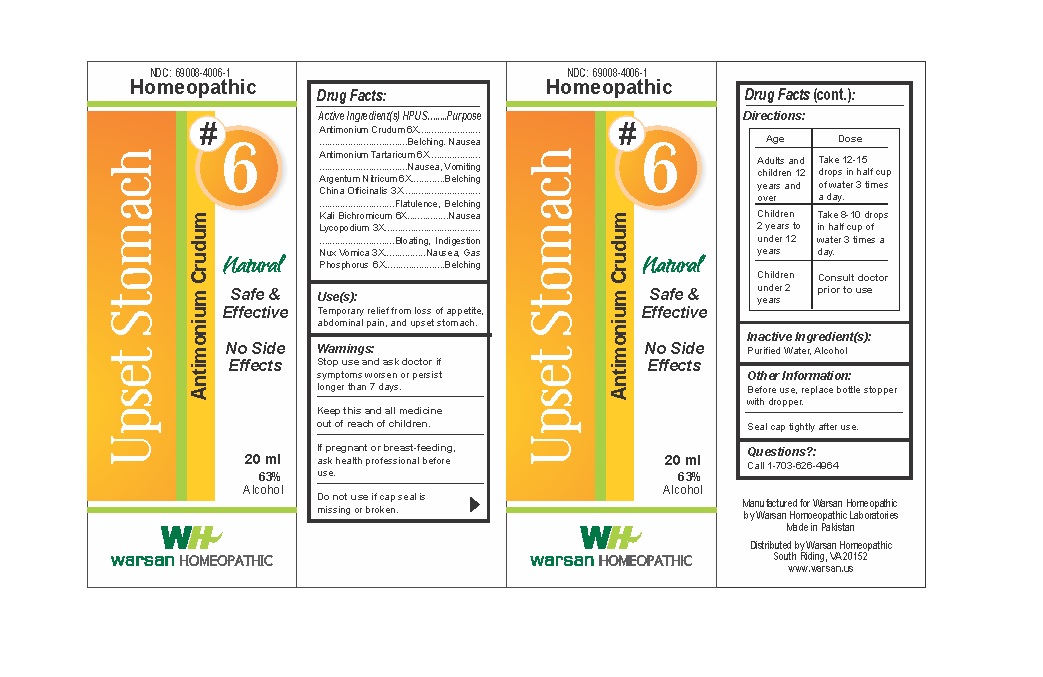 DRUG LABEL: Combination Remedy 6 - Upset Stomach
NDC: 69008-4006 | Form: SOLUTION/ DROPS
Manufacturer: Warsan Homoeopathic Laboratories
Category: homeopathic | Type: HUMAN OTC DRUG LABEL
Date: 20171225

ACTIVE INGREDIENTS: ANTIMONY TRISULFIDE 6 [hp_X]/1 mL; ANTIMONY POTASSIUM TARTRATE 6 [hp_X]/1 mL; SILVER NITRATE 6 [hp_X]/1 mL; CINCHONA OFFICINALIS BARK 3 [hp_X]/1 mL; POTASSIUM DICHROMATE 6 [hp_X]/1 mL; LYCOPODIUM CLAVATUM SPORE 3 [hp_X]/1 mL; STRYCHNOS NUX-VOMICA SEED 3 [hp_X]/1 mL; PHOSPHORUS 6 [hp_X]/1 mL
INACTIVE INGREDIENTS: ALCOHOL; WATER

Stop use and ask doctor if symptoms worsen or persist longer than 7 days.

If pregnant or breast-feeding, ask health professional before use.

Do not use if tamper evident seal is missing or broken.

Keep out of reach of children.

ACTIVE INGREDIENT

Antimonium Crudum 6X

Antimonium Tartaricum 6X

Argentum Nitricum 6X

China Officinalis 3X

Kali Bichromicum 6X

Lycopodium 3X

Nux Vomica 3X

Phosphorus 6X

PURPOSE

Temporary relief from loss of appetite, abdominal pain, and upset stomach

INACTIVE INGREDIENT

Purified Water

Alcohol

DOSAGE AND ADMINISTRATION

Adults and children 12 years and older: Take 10-15 drops in half cup of water 3 times a day.

Children 2 years to under 12 years: Take 8-10 drops in half cup of water of 3 times a day.

Children under 2 years: Consult doctor prior to use.

INDICATIONS AND USAGE

Temporary relief from loss of appetite, abdominal pain, and upset stomach